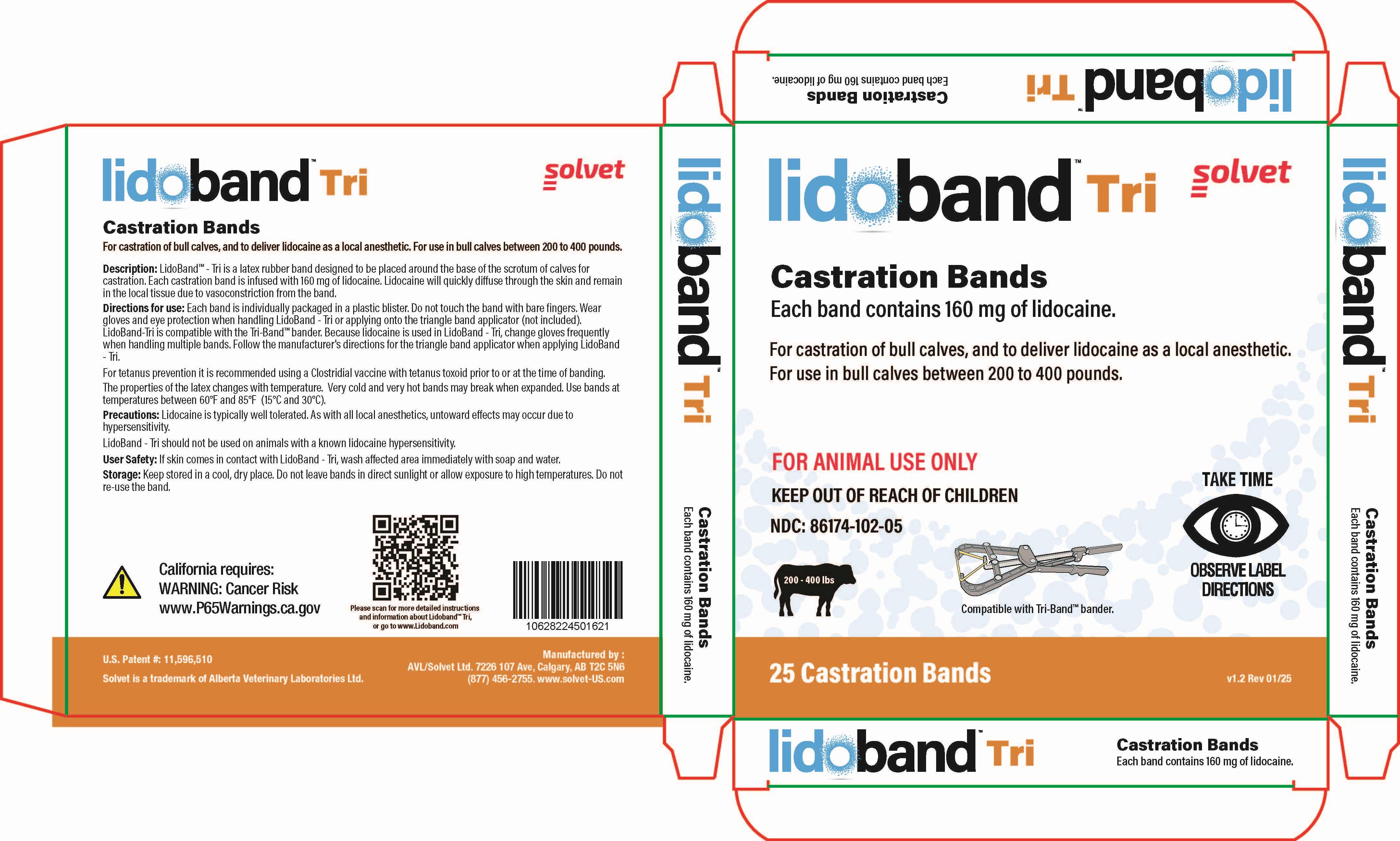 DRUG LABEL: LidoBand Tri
NDC: 86174-102 | Form: RING
Manufacturer: Alberta Veterinary Laboratories Ltd
Category: animal | Type: OTC ANIMAL DRUG LABEL
Date: 20251216

ACTIVE INGREDIENTS: LIDOCAINE 160 mg/1 1
INACTIVE INGREDIENTS: ISOPROPYL MYRISTATE 60 mg/1 1

LidoBand Tri Castration Bands

LidoBand Tri Castration Bands

Solvet

LidoBand Tri Castration Bands

Each band contains 160 mg of lidocaine.

For castration of bull calves, and to deliver lidocaine as a local anesthetic. For use in bull calves between 200 to 400 pounds.

FOR ANIMAL USE ONLY

KEEP OUT OF REACH OF CHILDREN

TAKE TIME OBSERVE LABEL DIRECTIONS

Description:

LidoBand™- Tri is a latex rubber band designed to be placed around the base of the scrotum of calves for castration. Each castration band is infused with 160 mg of lidocaine. Lidocaine will quickly diffuse through the skin and remain in the local tissue due to vasoconstriction from the band.

Precautions:

Lidocaine is typically well tolerated. As with all local anesthetics, untoward effects may occur due to hypersensitivity.

LidoBand- Tri should not be used on animals with a known lidocaine hypersensitivity.

User Safety:

If skin comes in contact with LidoBand - Tri, wash affected area immediately with soap and water.

Storage:

Keep stored in a cool, dry place.

Do not leave bands in direct sunlight or allow exposure to high temperatures.

Do not re-use the band.

Directions for use:

Each band is individually packaged in a plastic blister. Do not touch the band with bare fingers. Wear gloves and eye protection when handling LidoBand - Tri or applying onto the triangle band applicator (not included).

LidoBand - Tri is compatible with the Tri-Band™ bander. Because lidocaine is used in LidoBand - Tri, change gloves frequently when handling multiple bands. Follow the manufacturer's directions for the triangle band applicator when applying LidoBand - Tri.

For tetanus prevention it is recommended using a Clostridial vaccine with tetanus toxioid prior to or at the time of banding.

The properties of the latex changes with temperature. Very cold and very hot bands may break when expanded. Use bands at temperatures between 60°F and 85°F (15°C and 30°C).

Product Label:

LidoBand Tri Box of 25